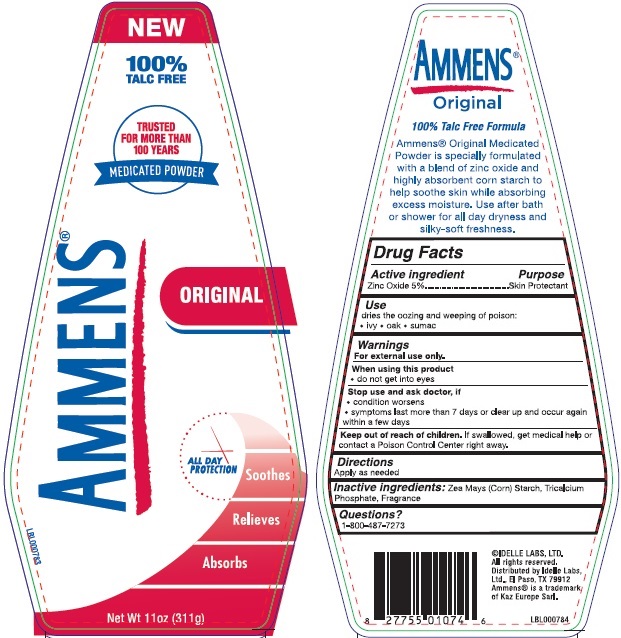 DRUG LABEL: Ammens Medicated Powder Original
NDC: 41595-1060 | Form: POWDER
Manufacturer: Idelle Labs, Ltd
Category: otc | Type: HUMAN OTC DRUG LABEL
Date: 20171229

ACTIVE INGREDIENTS: ZINC OXIDE 5 g/100 g
INACTIVE INGREDIENTS: STARCH, CORN; TRICALCIUM PHOSPHATE

AMMENS® MEDICATED POWDER - ORIGINAL

Active ingredient

Zinc Oxide 5%

Purpose

Skin Protectant

Use

dries the oozing and weeping of poison:

• ivy

• oak

• sumac

Warnings

For external use only.

When using this product

• do not get into eyes

Stop use and ask doctor, if

• condition worsens

• symptoms last more than 7 days or clear up and occur again within a few days

Keep out of reach of children.

If swallowed, get medical help or contact a Poison Control Center right away.

Directions

Apply as needed

Inactive ingredients:

Zea Mays (Corn) Starch, Tricalcium Phosphate, Fragrance

Questions?

call to 1-800-487-7273

©IDELLE LABS, LTD.
All rights reserved.
Distributed by Idelle Labs,
Ltd., El Paso, TX 79912
Ammens® is a trademark
of Kaz Europe Sarl.

PACKAGE LABEL.PRINCIPAL DISPLAY PANEL

AMMENS®

NEW 100% TALC FREE

TRUSTED FOR MORE THAN 100 YEARS

MEDICATED POWDER

ORIGINAL

Soothes

Relieves

Absorbs

Net Wt 11oz (311g)